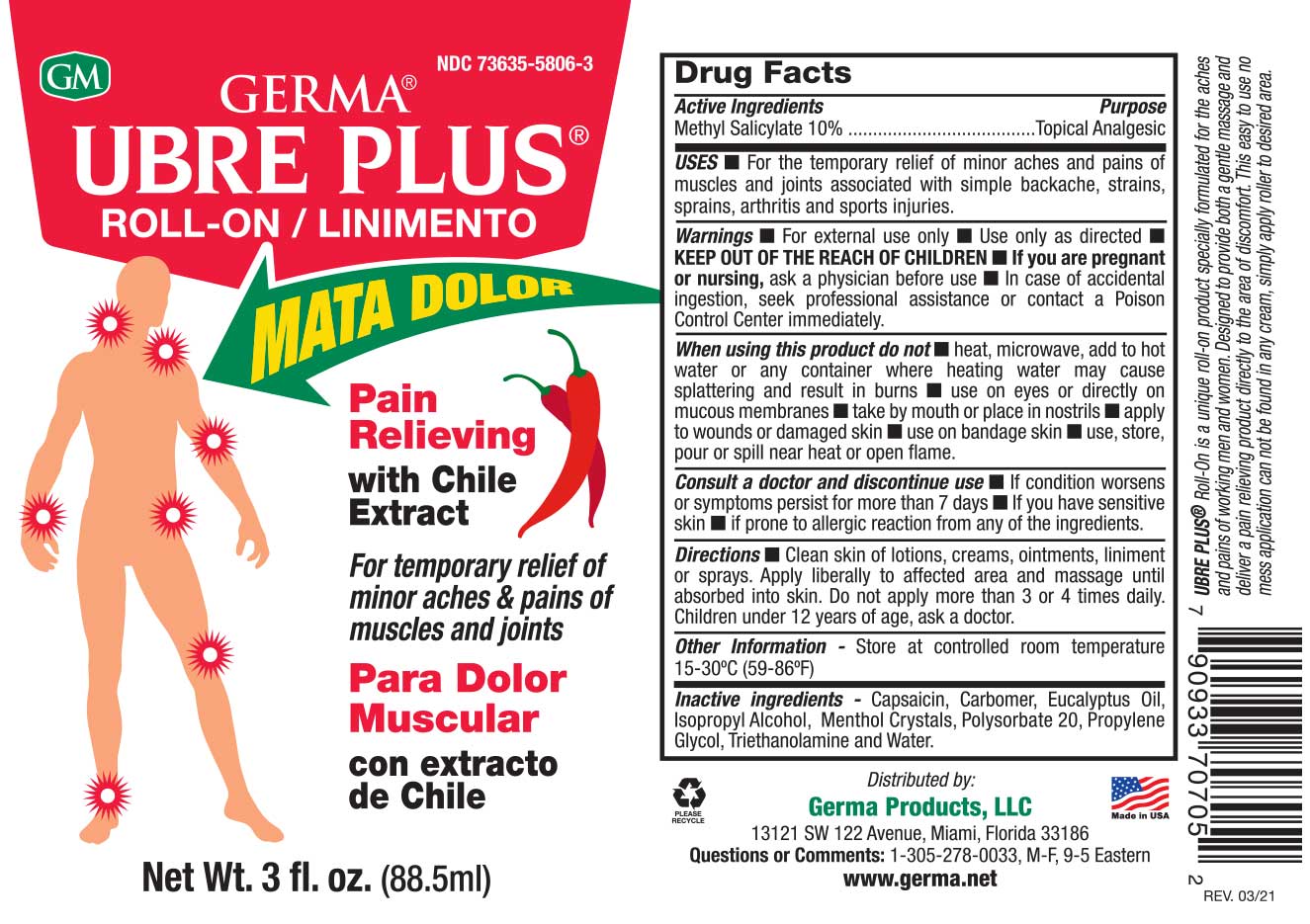 DRUG LABEL: Germa Linimento Ubre Plus (Roll-On)
NDC: 73635-5806 | Form: OINTMENT
Manufacturer: Germa Products, LLC
Category: otc | Type: HUMAN OTC DRUG LABEL
Date: 20251010

ACTIVE INGREDIENTS: METHYL SALICYLATE 100 mg/1 mL
INACTIVE INGREDIENTS: TROLAMINE; CAPSAICIN; MENTHOL; CARBOMER HOMOPOLYMER, UNSPECIFIED TYPE; WATER; EUCALYPTUS OIL; POLYSORBATE 20; PROPYLENE GLYCOL; ISOPROPYL ALCOHOL

Linimento Ubre Plus (Roll-On)

Active Ingredient

Methyl Salicylate 10%

Uses

For the temporary relief of minor aches and pains of muscles and joints associated with simple backache, strains, sprains, arthritis and sports injuries.

When using this product do not ■ heat, microwave, add to hot water or any container where heating water may cause splattering and result in burns ■ use on eyes or directly on mucous membranes ■ take by mouth or place in nostrils ■ apply to wounds or damaged skin ■ use on bandage skin ■ use, store, pour or spill near heat or open flame.

Purpose

Topical Analgesic

Warnings

For external use only ■ Use only as directed

Warnings

KEEP OUT OF THE REACH OF CHILDREN

In case of accidental ingestion, seek professional assistance or contact a Poison Control Center immediately.

PREGNANCY OR BREAST FEEDING

If pregnant or breast-feeding, ask a health professional before use.

ASK DOCTOR

Consult a doctor and discontinue use • If condition worsens or symptoms persist for more than 7 days • If you have sensitive skin • if prone to allergic reaction from any of the ingredients.

Other Information

Store at controlled room temperature 15-30ºC (59-86ºF)

Directions

Clean skin of lotions, creams, ointments, liniment or sprays. Apply liberally to affected area and massage until absorbed into skin. Do not apply more than 3 or 4 times daily. Children under 12 years of age, ask a doctor.

Inactive Ingredients

Capsaicin, Carbomer, Eucalyptus Oil, Isopropyl Alcohol, Menthol Crystals, Polysorbate 20, Propylene Glycol, Triethanolamine and Water.